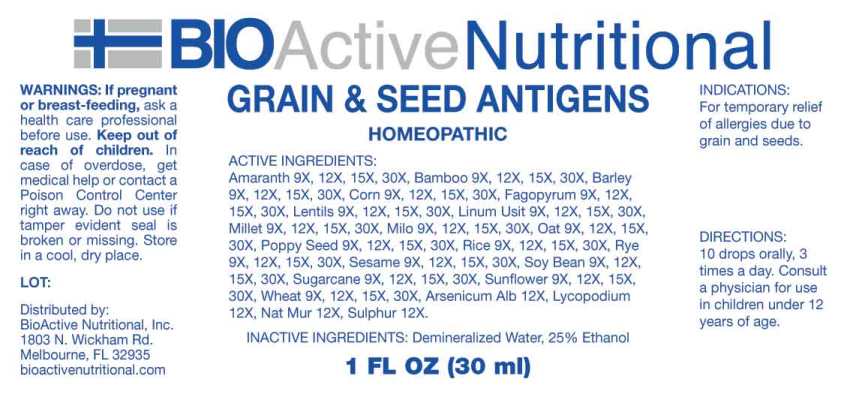 DRUG LABEL: Grain and Seed Antigens
NDC: 43857-0566 | Form: LIQUID
Manufacturer: BioActive Nutritional, Inc.
Category: homeopathic | Type: HUMAN OTC DRUG LABEL
Date: 20230622
DEA Schedule: CII

ACTIVE INGREDIENTS: BAMBUSA VULGARIS LEAF 9 [hp_X]/1 mL; BARLEY 9 [hp_X]/1 mL; POPPY SEED 9 [hp_X]/1 mL; CORN 9 [hp_X]/1 mL; FLAX SEED 9 [hp_X]/1 mL; BUCKWHEAT 9 [hp_X]/1 mL; MILLET 9 [hp_X]/1 mL; SORGHUM BICOLOR WHOLE 9 [hp_X]/1 mL; OAT 9 [hp_X]/1 mL; BROWN RICE 9 [hp_X]/1 mL; RYE 9 [hp_X]/1 mL; LENTIL 9 [hp_X]/1 mL; SESAME SEED 9 [hp_X]/1 mL; AMARANTH 9 [hp_X]/1 mL; SOYBEAN 9 [hp_X]/1 mL; SUGARCANE 9 [hp_X]/1 mL; SUNFLOWER SEED 9 [hp_X]/1 mL; WHEAT 9 [hp_X]/1 mL; ARSENIC TRIOXIDE 12 [hp_X]/1 mL; LYCOPODIUM CLAVATUM SPORE 12 [hp_X]/1 mL; SODIUM CHLORIDE 12 [hp_X]/1 mL; SULFUR 12 [hp_X]/1 mL
INACTIVE INGREDIENTS: WATER; ALCOHOL

DRUG FACTS:

ACTIVE INGREDIENTS:

Bamboo 9X, 12X, 15X, 30X, Barley 9X, 12X, 15X, 30X, Poppy Seed 9X, 12X, 15X, 30X, Corn 9X, 12X, 15X, 30X, Flax Seed 9X, 12X, 15X, 30X, Buckwheat 9X, 12X, 15X, 30X, Millet 9X, 12X, 15X, 30X, Milo 9X, 12X, 15X, 30X, Oat 9X, 12X, 15X, 30X, Rice 9X, 12X, 15X, 30X, Rye 9X, 12X, 15X, 30X, Lentils 9X, 12X, 15X, 30X, Sesame 9X, 12X, 15X, 30X, Amaranth 9X, 12X, 15X, 30X, Soy Bean 9X, 12X, 15X, 30X, Sugarcane 9X, 12X, 15X, 30X, Sunflower Seed 9X, 12X, 15X, 30X, Wheat 9X, 12X, 15X, 30X, Arsenicum Album 12X, Lycopodium Clavatum 12X, Natrum Muriaticum 12X, Sulphur 12X.

INDICATIONS:

For temporary relief of allergies due to grain and seeds.

WARNINGS:

If pregnant or breast-feeding, ask a health care professional before use.

Keep out of reach of children. In case of overdose, get medical help or contact a Poison Control Center right away.

Do not use if tamper evident seal is broken or missing.

Store in cool, dry place.

Keep out of reach of children. In case of overdose, get medical help or contact a Poison Control Center right away.

DIRECTIONS:

10 drops orally, 3 times a day. Consult a physician for use in children under 12 years of age.

INDICATIONS:

For temporary relief of allergies due to grain and seeds.

INACTIVE INGREDIENTS:

Demineralized Water, 25% Ethanol

QUESTIONS:

Distributed by:
BioActive Nutritional, Inc.
1803 N. Wickham Rd.
Melbourne, FL 32935
bioactivenutritional.com

PACKAGE LABEL DISPLAY:

BIOActive Nutritional

Grain & See Antigens

HOMEOPATHIC

1 FL OZ (30 ml)